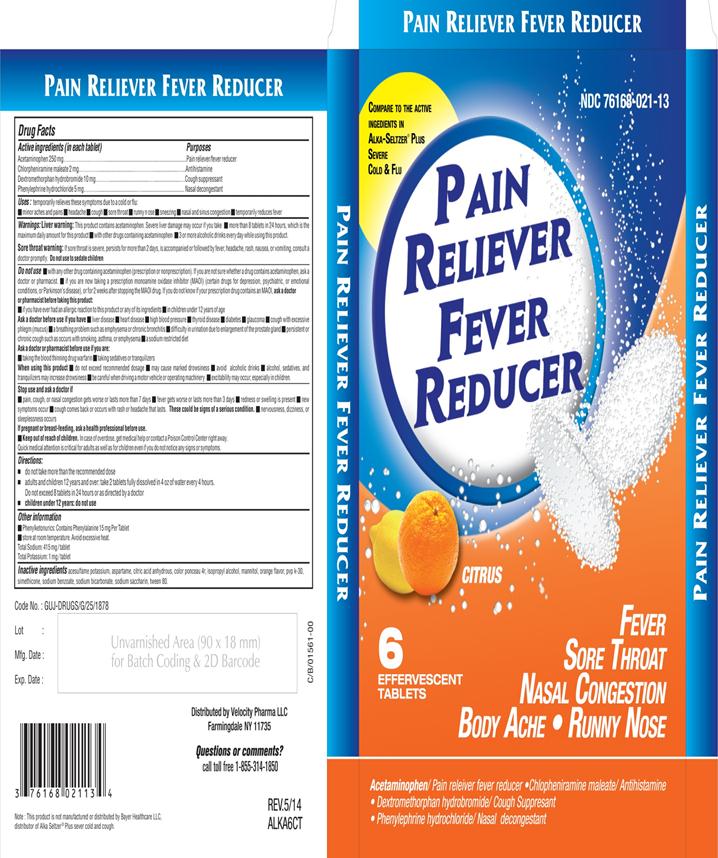 DRUG LABEL: Pain Reliever Fever Reducer
NDC: 76168-021 | Form: TABLET, EFFERVESCENT
Manufacturer: Velocity Pharma
Category: otc | Type: HUMAN OTC DRUG LABEL
Date: 20140824

ACTIVE INGREDIENTS: ACETAMINOPHEN 250 mg/1 1; DEXTROMETHORPHAN HYDROBROMIDE 10 mg/1 1; PHENYLEPHRINE HYDROCHLORIDE 5 mg/1 1; CHLORPHENIRAMINE MALEATE 2 mg/1 1
INACTIVE INGREDIENTS: ACESULFAME POTASSIUM; ASPARTAME; ANHYDROUS CITRIC ACID; PONCEAU 4R; ISOPROPYL ALCOHOL; MANNITOL; ORANGE; POVIDONE K30; DIMETHICONE; SODIUM BENZOATE; SODIUM BICARBONATE; SACCHARIN SODIUM; POLYSORBATE 80

Acetaminophen, Chlorpheniramine maleate, Dextromethorphan HBrand Phenylephrine HCl

Active Ingredient

(in each tablet)

Acetaminophen 250 mg

Chlorpheniramine Maleate 2mg

Dextromethorphan HBr 10 mg

Phenylephrine HCl 5 mg

Purpose

pain reliever/fever reducer

Antihistamine

Cough Suppressant

Nasal decongestant

Uses

Temporarily relieves these symptoms due to cold or flu:

- Minor aches and pains
- Headaches
- Cough
- Sore throat
- Runny nose
- Sneezing
- Nasal and sinus congestion
- Temporarily reduces fever

Warnings

Liver Warning: This product contains acetaminophen. Severe liver damage may occur if you take

- more than 8 tablets in 24 hours which is maximum daily amount for this product
- with other drugs containing acetaminophen
- 3 or more alcoholic drinks daily while using this product

Sore throat waring: If sore throat is sever, persists for more than 2 days, is accompanied or followed by fever, headache, rash, nausea or vomiting consult a doctor promptly. Do not use to sedate children.

do not use:

- with any other drug containing acetaminophen (prescription or not prescription). If you are not sure whether a drug contains acetaminophen, ask a doctor or pharmacist.
- if you are now taking a prescription monoamine oxidase inhibitor (MAOI) (Certain drugs for depression, psychiatric or emotional conditions or Parkinson’s disease), or for 2 weeks after stopping the MAOI drug, If you do not know if your prescription drug contains an MAOI, ask a doctor or pharmacist before taking this product.

Ask a doctor before use if you have

- liver disease
- Heart disease
- Thyroid disease
- Diabetes
- High blood pressure
- Glaucoma
- Cough with excessive phlegm (mucus)
- A breathing problem such as emphysema or chronic bronchitis
- Difficulty in urinating due to enlargement of prostate gland
- Persistent or chronic cough such as occurs with smoking, asthma or emphysema
- A sodium restricted diet

ask your doctor or pharmacist before use if you are

- taking the blood thinning drug warfarin.
- taking sedative or tranquilizers

when using this product

- do not exceed recommended dosage
- may cause marked drowsiness
- avoid alcoholic drinks
- alcohol, sedative and tranquilizers may increase drowsiness
- be careful when driving a motor vehicle or operating machinery
- excitability may occur especially in children

Stop use and ask a doctor if

- pain, cough or nasal congestion gets worse or lasts more than 7 days
- fever gets worse or lasts more than 3 days
- redness or swelling is present
- new symptoms occur
- cough comes back or occurs with rash or headache that lasts. These could be signs of serious condition.
- Nervousness, dizziness, or sleeplessness occurs
- If pregnant or breast-feeding, ask a health professional before use

Keep out of reach of children.

Overdose warning: Taking more than recommended dose (overdose) may cause liver damage. In case of overdose, get medical help or contact a Poison Control Center right away. Prompt medical attention is critical for adults as well as for children even if you do not notice any signs or symptoms.

Direction

- do not take more than the recommended dose
- Adults and children 12 years and over: 2 tablets fully dissolved in 4 oz of water every 4 hours, Do not exceed 8 tablets in 24 hours or as directed by a doctor
- children under 12 years: do not use

Other Information

- phenylketonurics: contains phenylalanine 15 mg per tablet
- store at room temperature , avoid excessive heat.

Total sodium : 415 mg/tablet
Total potassium: 1mg /tablet

INACTIVE INGREDIENT

acesulfame potassium, aspartame, citric acid anhydrous, color ponceau 4r, isopropyl alcohol, mannitol, orange flavor, pvp k-30, Simethicone, sodium benzoate, sodium bicarbonate, sodium saccharin, tween 80.

QUESTIONS

Call toll free 1-855-314-1850

Distributed by Velocity Pharma Llc

PACKAGE LABEL.PRINCIPAL DISPLAY PANEL

NDC: 76168-021-13 6 tablets